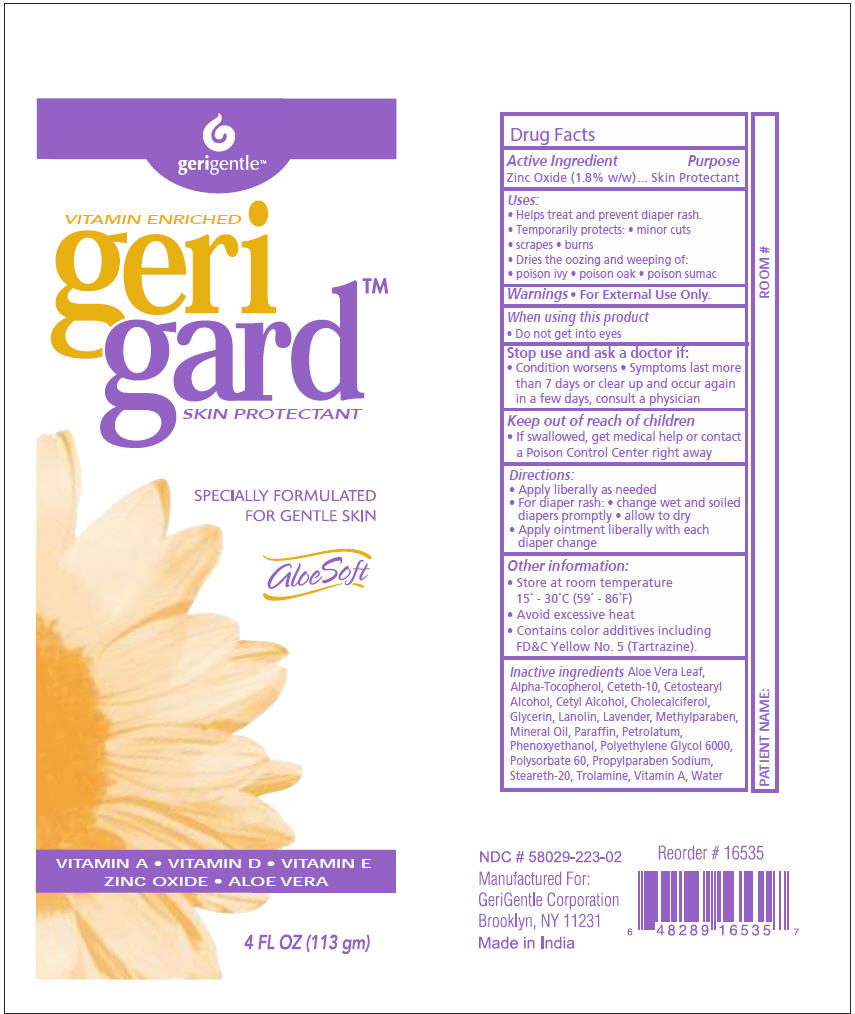 DRUG LABEL: Gerigard-Skin Protectant
NDC: 69771-108 | Form: OINTMENT
Manufacturer: Geri-Gentle Corporation
Category: otc | Type: HUMAN OTC DRUG LABEL
Date: 20180118

ACTIVE INGREDIENTS: Zinc Oxide 1.8 g/100 g
INACTIVE INGREDIENTS: Aloe Vera Leaf; .Alpha.-Tocopherol; Ceteth-10; Cetostearyl Alcohol; Cetyl Alcohol; Cholecalciferol; Glycerin; Lanolin; Methylparaben; Mineral Oil; Paraffin; Petrolatum; Phenoxyethanol; Polyethylene Glycol 6000; Polysorbate 60; Propylparaben Sodium; Steareth-20; Trolamine; Vitamin A; Water

Gerigard™-Skin Protectant

Drug Facts

Active Ingredient

Zinc Oxide (1.8% w/w)

Purpose

Skin Protectant

Uses

- Helps treat and prevent diaper rash.
- Temporarily protects:
  - minor cuts
  - scrapes
  - burns
- Dries the oozing and weeping of:
  - poison ivy
  - poison oak
  - poison sumac

Warnings

- For External Use Only.

When using this product

- Do not get into eyes

Stop use and ask a doctor if

- Condition worsens
- Symptoms last more than 7 days or clear up and occur again in a few days, consult a physician

Keep out of reach of children

- If swallowed, get medical help or contact a Poison Control Center right away

Directions

- Apply liberally as needed
- For diaper rash:
  - change wet and soiled diapers promptly
  - allow to dry
- Apply ointment liberally with each diaper change

Other information

- Store at room temperature 15° - 30°C (59° - 86°F)
- Avoid excessive heat
- Contains color additives including FD&C Yellow No. 5 (Tartrazine).

Inactive ingredients

Aloe Vera Leaf, Alpha-Tocopherol, Alcohol, Cetyl Alcohol, Cholecalciferol, Glycerin, Lanolin, Lavender Mineral Oil, Paraffin, Petrolatum, Phenoxyethanol, Polyethylene Glycol 6000, Polysorbate 60, Propylparaben Sodium, Steareth-20, Ceteth-10, Cetostearyl , Methylparaben, Trolamine, Vitamin A, Water

PRINCIPAL DISPLAY PANEL - 113 gm Tube Label

gerigentle™

VITAMIN ENRICHED
geri
gard™
SKIN PROTECTANT

SPECIALLY FORMULATED
FOR GENTLE SKIN

AloeSoft

VITAMIN A • VITAMIN D • VITAMIN E
ZINC OXIDE • ALOE VERA

4 FL OZ (113 gm)